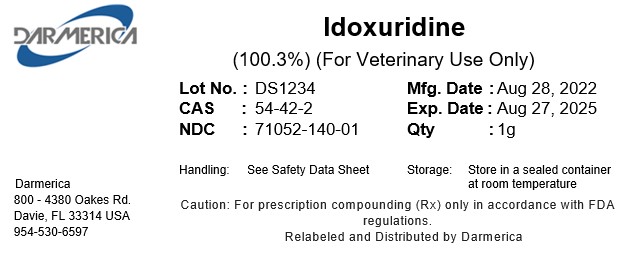 DRUG LABEL: Idoxuridine
NDC: 71052-140 | Form: POWDER
Manufacturer: DARMERICA, LLC
Category: other | Type: BULK INGREDIENT - ANIMAL DRUG
Date: 20240930

ACTIVE INGREDIENTS: Idoxuridine 1 kg/1 kg

Idoxuridine